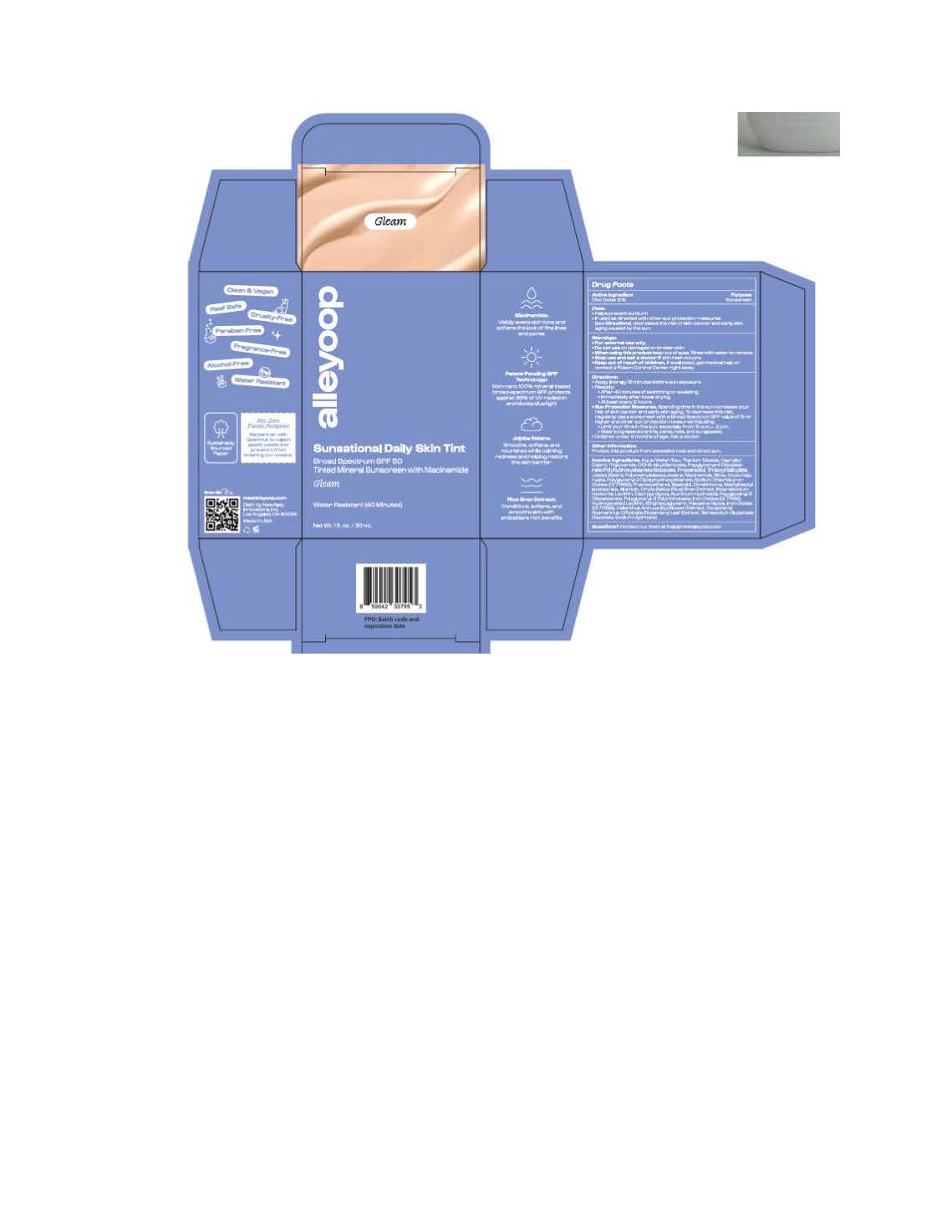 DRUG LABEL: Alleyoop Sunsational Broad Spectrum
NDC: 84830-2431 | Form: LOTION
Manufacturer: NewAlley Innovations Inc
Category: otc | Type: HUMAN OTC DRUG LABEL
Date: 20250924

ACTIVE INGREDIENTS: ZINC OXIDE 132 mg/1 mL
INACTIVE INGREDIENTS: NIACINAMIDE; WATER; PROPANEDIOL; SODIUM CHLORIDE; POLYGLYCERYL-4 DIISOSTEARATE/POLYHYDROXYSTEARATE/SEBACATE; LECITHIN, SOYBEAN; CAPRYLYL GLYCOL; SODIUM HYDROXIDE; FERRIC OXIDE YELLOW; TETRASODIUM GLUTAMATE DIACETATE; TITANIUM DIOXIDE; ROSMARINUS OFFICINALIS WHOLE; METHYLHEPTYL ISOSTEARATE; POLYGLYCERYL-3 DIISOSTEARATE; STEARALKONIUM HECTORITE; ORYZA SATIVA WHOLE; SILICON DIOXIDE; COCO-CAPRYLATE; TOCOPHEROL; POLYMETHYLSILSESQUIOXANE (4.5 MICRONS); MICA; .ALPHA.-BISABOLOL, (+)-; TRIDECYL SALICYLATE; ALLANTOIN; FERRIC OXIDE RED; HYDROLYZED JOJOBA ESTERS (ACID FORM); CALCIUM SODIUM BOROSILICATE; DIMETHICONE 100; PHENOXYETHANOL; HEXYLENE GLYCOL; ETHYLHEXYLGLYCERIN; POLYGLYCERYL-2 DIPOLYHYDROXYSTEARATE; ALKYL (C12-15) BENZOATE; HELIANTHUS ANNUUS WHOLE

Alleyoop Sunsational Broad Spectrum